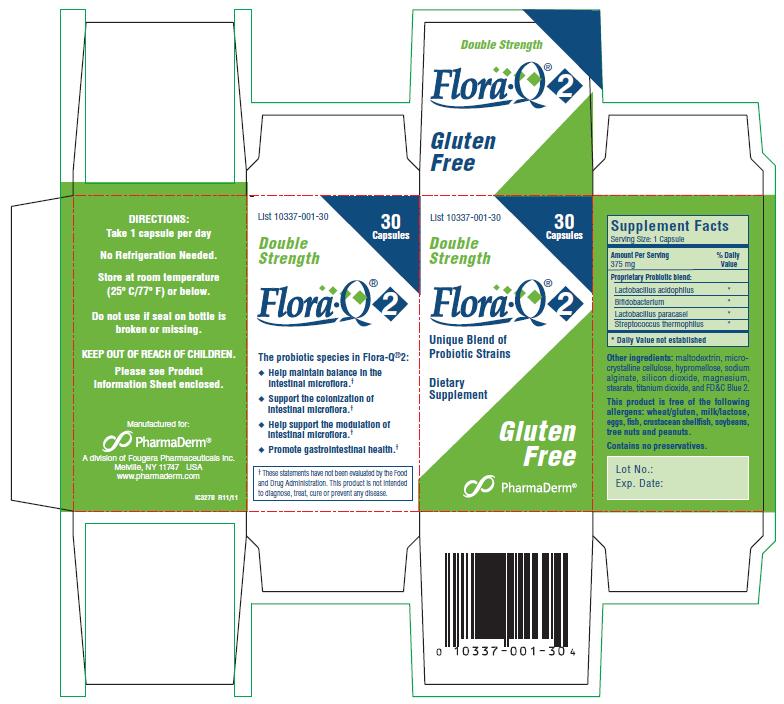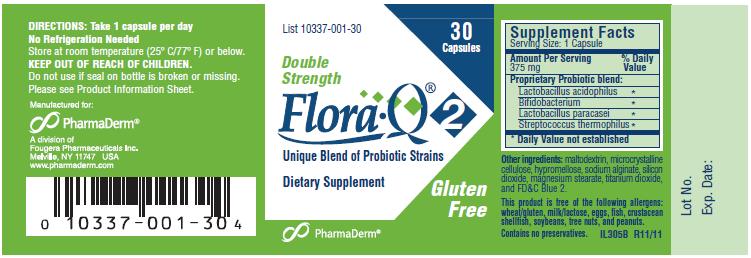 DRUG LABEL: Flora Q2
NDC: 10337-001 | Form: CAPSULE
Manufacturer: PharmaDerm A division of Fougera Pharmaceuticals Inc.
Category: other | Type: DIETARY SUPPLEMENT
Date: 20120507

ACTIVE INGREDIENTS: lactobacillus acidophilus 16000000000 [CFU]/1 1
INACTIVE INGREDIENTS: maltodextrin; hypromelloses; cellulose, microcrystalline; sodium alginate; silicon dioxide; magnesium stearate; titanium dioxide; FD&C BLUE NO. 2

Flora•Q®2
Double Strength
Unique Blend of Probiotic Strains
Dietary Supplement
Gluten Free
BRAND NAME: Flora•Q®2

STATEMENT OF IDENTITY

PRODUCT DESCRIPTION: Off-white capsules, each containing 300 mg* of a standardized, light-beige colored powder consisting of an aggregate of a minimum of 16 billion CFU (16 x 10^9 Colony Forming Units) freeze-dried cultures at time of manufacture of species listed below.

Guaranteed potency of no less than 8 billion CFU freeze-dried cultures at expiration date.

* Based on an estimated tapped density of 0.7 g/mL.

Also contains: maltodextrin, hypromellose, microcrystalline cellulose, sodium alginate, silicon dioxide, magnesium stearate, titanium dioxide, and FD&C Blue 2.

Each capsule, containing a proprietary probiotic blend and other ingredients, is equivalent to 375 mg per serving.

This product is free of the following allergens: wheat/gluten, milk/lactose, eggs, fish, crustacean shellfish, soybeans, tree nuts, and peanuts.

Contains no preservatives.

GENERIC NAME:

Lactobacillus acidophilus

Bifidobacterium

Lactobacillus paracasei

Streptococcus thermophilus

HEALTH CLAIM

COMMON USES: This probiotic is used to help maintain the normal bacterial balance of the gastrointestinal tract.†

THE PROBIOTIC SPECIES IN FLORA• Q®2:

- Help maintain balance in the intestinal microflora.†
- Support the colonization of intestinal microflora.†
- Help support the modulation of intestinal microflora.†
- Promote gastrointestinal health.†

†These statements have not been evaluated by the Food and Drug Administration. This product is not intended to diagnose, treat, cure or prevent any disease.

PRECAUTIONS

HOW TO USE: Use this product as directed on the package, unless instructed differently by your doctor.

CAUTIONS: Before you begin taking any dietary supplement, check with your doctor or pharmacist.

KEEP OUT OF THE REACH OF CHILDREN.

POSSIBLE SIDE EFFECTS: Potential side effects that may dissipate include increased stomach gas. If this occurs and is bothersome, check with your doctor. Should you experience symptoms of an allergic reaction, including rash, itching, swelling, dizziness or trouble breathing, contact your doctor, nurse or pharmacist immediately.

DOSAGE AND ADMINISTRATION

DIRECTIONS: Take one capsule per day. May be taken with or without food.

SAFE HANDLING WARNING

HOW SUPPLIED: Off-white capsules imprinted Flora• Q®2 are supplied in bottles of 30 (List 10337-001-30).

STORAGE: Potency guaranteed through expiration date on package when stored at room temperature (25º C/77º F) or below. DO NOT STORE IN THE BATHROOM. Keep container closed. No refrigeration needed.

Do not use if seal on bottle is broken or missing.

Manufactured for:
PharmaDerm®
A divisdion of
Fougera
PHARMEUTICALS INC.
Melville, New York 11747
www.pharmaderm.com

IL306B R11/11

Principal Display Panel – Carton Label

List 10337-001-30

30
Capsules

Double Strength

Flora•Q®2

Unique Blend
of Probiotic Strains

Dietary Supplement

Gluten Free

PharmaDerm®

Principal Display Panel – Bottle Label

List 10337-001-30

30 Capsules

Double Strength

Flora•Q®2

Unique Blend
of Probiotic Strains

Dietary Supplement

Gluten Free

PharmaDerm®